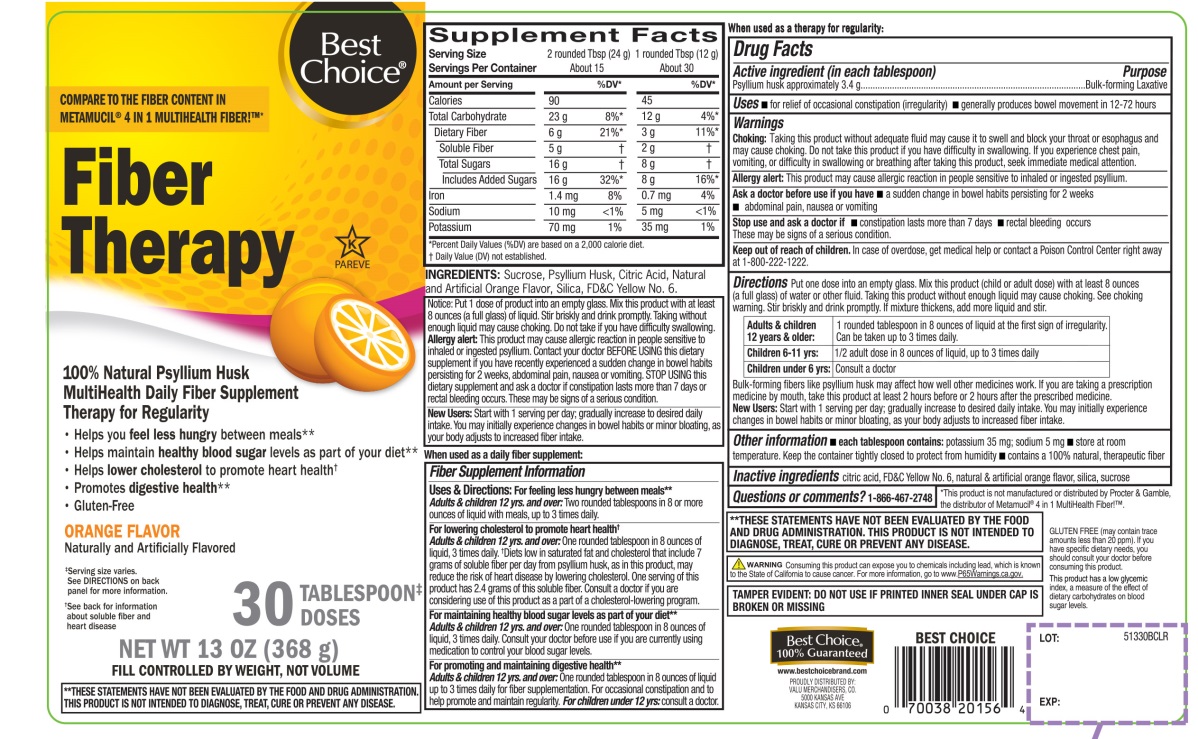 DRUG LABEL: Best Choice Fiber Therapy

NDC: 63941-513 | Form: POWDER
Manufacturer: BEST CHOICE (VALU MERCHANDISERS COMPANY)
Category: otc | Type: HUMAN OTC DRUG LABEL
Date: 20250716

ACTIVE INGREDIENTS: PSYLLIUM HUSK 3.4 g/12 g
INACTIVE INGREDIENTS: ANHYDROUS CITRIC ACID; FD&C YELLOW NO. 6; SILICON DIOXIDE; SUCROSE

Best Choice Natural Psyllium Husk Orange Flavor 30 tablespoon Doses

Drug Facts

Active ingredient: (in each tablespoon)

Psyllium husk approximately 3.4 g

Purpose

Bulk-forming laxative

Uses:

- for relief of occasional constipation (irregularity)
- generally produces bowel movement in 12-72 hours

Warnings:

Choking:

Taking this product without adequate fluid may cause it to swell and block your throat or esophagus and may cause choking. Do not take this product if you have difficulty in swallowing. If you experience chest pain, vomiting, or difficulty in swallowing or breathing after taking this product, seek immediate medical attention.

Allergy alert:

This product may cause allergic reaction in people sensitive to inhaled or ingested psyllium.

Ask a doctor before use if you have

- a sudden change in bowel habits persisting for 2 weeks
- abdominal pain, nausea or vomiting

Stop use and ask a doctor if

- constipation lasts more than 7 days
- rectal bleeding occurs

These may be signs of a serious condition.

Keep out of reach of children.In case of overdose, get medical help or contact a Poison Control Center right away at 1-800-222-1222.

Directions:

Put one dose into an empty glass. Mix this product (child or adult dose) with at least 8 ounces (a full glass) of water or other fluid. Taking this product without enough liquid may cause choking. See choking warning. Stir briskly and drink promptly. If mixture thickens, add more liquid and stir.

Adults & children 12 years & older: | 1 rounded tablespoon in 8 ounces of liquid at the first sign of irregularity. Can be taken up to 3 times daily.
Children 6-11 yrs : | ½ adult dose in 8 ounces of liquid, up to 3 times daily
Children under 6 yrs: | Consult a doctor

Bulk-forming fibers like psyllium husk may affect how well other medicines work. If you are taking a prescription medicine by mouth, take this product at least 2 hours before or 2 hours after the prescribed medicine.

New Users:

Start with 1 serving per day; gradually increased to desired daily intake. You may initially experience changes in bowel habits or minor bloating, as your body adjusts to increased fiber intake.

Other information:

- each tablespoon contains:potassium 35 mg; sodium 5 mg
- store at room temperature. Keep the container tightly closed to protect from humidity
- contains a 100% natural, therapeutic fiber

Inactive ingredients:

citric acid, FD&C Yellow No. 6, natural and artificial orange flavor, silica, sucrose.

Questions or comments?

1-866-467-2748

PRINCIPAL DISPLAY PANEL

Best Choice®

NDC 63941-513-30

COMPARE TO THE FIBER CONTENT IN METAMUCIL®4 IN 1 MULTIHEALTH FIBER!™*

Fiber Therapy

100% Natural Psyllium Husk

MultiHealth Daily Fiber Supplement Therapy for Regularity

- Helps you feel less hungrybetween meals**
- Helps maintain healthy blood sugarlevels as part of your diet **
- Helps lower cholesterolto promote heart health†
- Promotes digestive health**
- Gluten free

ORANGE FLAVOR

Naturally and Artificially Flavored

30 TABLESPOON DOSES‡

NET WT 13 OZ (368 g)

FILL CONTROLLED BY WEIGHT, NOT VOLUME

K PAREVE

‡Serving size varies See DIRECTIONS on back panel for more information

†See back for information about soluble fiber and heart disease.

**THESE STATEMENTS HAVE NOT BEEN EVALUATED BY THE FOOD AND DRUG ADMINISTRATION. THIS PRODUCT IS NOT INTENDED TO DIAGNOSE, TREAT, CURE OR PREVENT ANY DISEASE.

TAMPER EVIDENT: DO NOT USE IF PRINTED INNER SEAL IS BROKEN OR MISSING

WARNING:Consuming this product can expose you to chemicals including lead, which is known to the State of California to cause cancer. For more information go to www.P65Warningd.ca.gov.

*This product is not manufactured or distributed by Procter & Gamble, the distributor of Metamucil®4 in 1 MultiHealth Fiber!™.

GLUTEN FREE if you have specific dietary needs, you should consult your doctor before consuming this product.

This product has a low glycemic index, a measure of the effect of dietary carbohydrates on blood sugar levels.

Best Choice®100% Guaranteed

www.bestchoicebrand.com

PROUDLY DISTRIBUTED BY:

VALU MERCHANDISERS, CO.

5000 KANSAS AVE

KANSAS CITY, KS 66106

BEST CHOICE